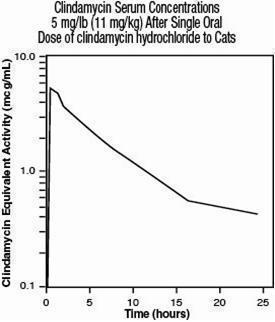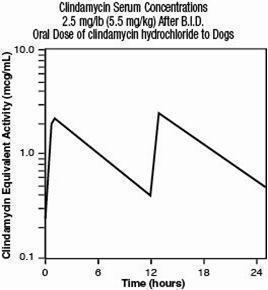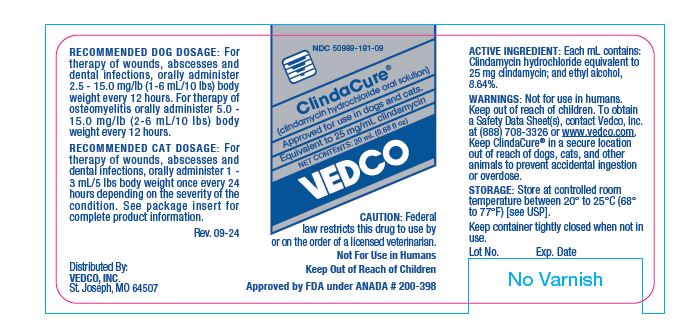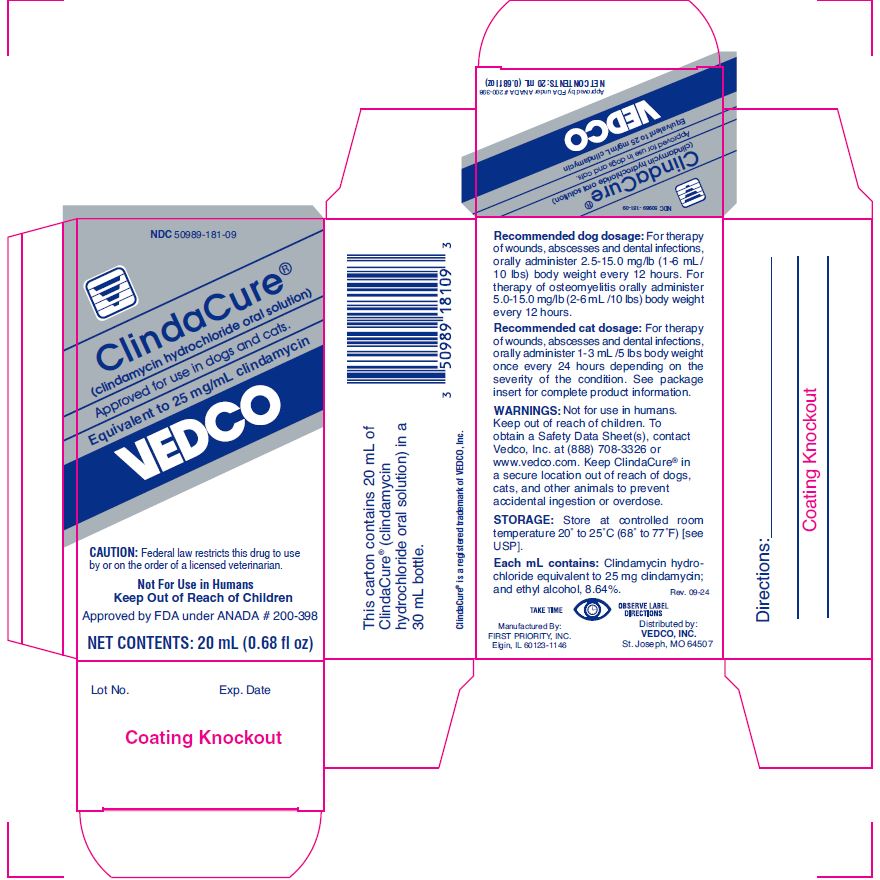 DRUG LABEL: ClindaCure
NDC: 50989-181 | Form: LIQUID
Manufacturer: VEDCO
Category: animal | Type: PRESCRIPTION ANIMAL DRUG LABEL
Date: 20241209

ACTIVE INGREDIENTS: CLINDAMYCIN HYDROCHLORIDE 25 mg/1 mL

ClindaCure®
(clindmycin hydrochloride liquid)

WARNINGS AND PRECAUTIONS

Approved for use in dogs and cats.

Equivalent to 25 mg/mL clindamycin

NET CONTENTS: 20 mL (0.68 fl oz)

Caution: Federal law restricts this drug to use by or on the order of a licensed veterinarian.

Not For Use in Humans
Keep Out of Reach of Children

DESCRIPTION

Clindamycin Hydrochloride Oral Drops (clindamycin hydrochloride liquid) contains clindamycin hydrochloride which is the hydrated salt of clindamycin. Clindamycin is a semisynthetic antibiotic produced by a 7(S)-chlorosubstitution of the 7(R)-hydroxyl group of a naturally produced antibiotic produced by Streptomyces lincolnensis var. lincolnensis.

Clindamycin Hydrochloride Oral Drops (For Use in Dogs and Cats) is a palatable formulation intended for oral administration. Each mL of Clindamycin Hydrochloride Oral Drops contains clindamycin hydrochloride equivalent to 25 mg clindamycin; and ethyl alcohol, 8.64%.

INDICATIONS

Clindamycin Hydrochloride Oral Drops (for use in dogs and cats) is indicated for the treatment of infections caused by susceptible strains of the designated microorganisms in the specific conditions listed below:

DOGS:

Skin infections (wounds and abscesses) due to coagulase positive staphylococci (Staphylococcus aureus or Staphylococcus intermedius). Deep wounds and abscesses due to Bacteroides fragilis, Prevotella melaninogenicus, Fusobacterium necrophorum and Clostridium perfringens. Dental infections due to Staphylococcus aureus, Bacteroides fragilis, Prevotella melaninogenicus, Fusobacterium necrophorum and Clostridium perfringens. Osteomyelitis due to Staphylococcus aureus, Bacteroides fragilis, Prevotella melaninogenicus, Fusobacterium necrophorum and Clostridium perfringens.

CATS:

Skin infections (wounds and abscesses) due to Staphylococcus aureus, Staphylococcus intermedius and Streptococcus spp. Deep wounds and infections due to Clostridium perfringens and Bacteroides fragilis. Dental infections due to Staphylococcus aureus, Staphylococcusintermedius, Streptococcus spp., Clostridium perfringens and Bacteroides fragilis.

DOSAGE AND ADMINISTRATION

Dogs:

Infected Wounds, Abscesses and Dental Infections

Oral: 2.5 - 15.0 mg/lb body weight every 12 hours.

Duration: Treatment with Clindamycin Hydrochloride Oral Drops products may be continued up to a maximum of 28 days if clinical judgment indicates. Treatment of acute infections should not be continued for more than three or four days if no response to therapy is seen.

Dosage Schedule:

Oral Solution

Clindamycin Hydrochloride Oral Drops, administer 1-6 mL/10 lbs body weight every 12 hours.

Dogs:

Osteomyelitis

Oral: 5.0-15.0 mg/lb body weight every 12 hours.

Duration: Treatment with Clindamycin Hydrochloride Oral Drops is recommended for a minimum of 28 days. Treatment should not be continued for longer than 28 days if no response to therapy is seen.

Dosage Schedule:

Oral Solution

Clindamycin Hydrochloride Oral Drops, administer 2-6 mL/10 lbs body weight every 12 hours.

Cats:

Infected Wounds, Abscesses and Dental Infections

5.0 - 15.0 mg/lb body weight once every 24 hours depending on the severity of the condition.

Duration: Treatment with Clindamycin Hydrochloride Oral Drops may be continued up to a maximum of 14 days if clinical judgment indicates. Treatment of acute infections should not be continued for more than three to four days if no clinical response to therapy is seen.

Dosage Schedule:

Clindamycin Hydrochloride Oral Drops, to provide 5.0 mg/lb, administer 1 mL/5 lbs body weight once every 24 hours; to provide 15.0 mg/lb, administer 3 mL/5 lbs body weight once every 24 hours.

CONTRAINDICATIONS

Clindamycin Hydrochloride Oral Drops is contraindicated in animals with a history of hypersensitivity to preparations containing clindamycin or lincomycin.

Because of potential adverse gastrointestinal effects, do not administer to rabbits, hamsters, guinea pigs, horses, chinchillas or ruminating animals.

WARNINGS

Not for use in humans. Keep out of reach of children. To obtain a Safety Data Sheet(s), contact Vedco, Inc. at (888) 708-3326 or www.vedco.com. Keep ClindaCure® in a secure location out of reach of dogs, cats, and other animals to prevent accidental ingestion or overdose.

PRECAUTIONS

During prolonged therapy of one month or greater, periodic liver and kidney function tests and blood counts should be performed.

The use of Clindamycin Hydrochloride Oral Drops occasionally results in overgrowth of non-susceptible organisms such as clostridia and yeasts. Therefore, the administration of Clindamycin Hydrochloride Oral Drops should be avoided in those species sensitive to the gastrointestinal effects of clindamycin (see CONTRAINDICATIONS). Should superinfections occur, appropriate measures should be taken as indicated by the clinical situation.

Patients with very severe renal disease and/or very severe hepatic disease accompanied by severe metabolic aberrations should be dosed with caution, and serum clindamycin levels monitored during high-dose therapy.

Clindamycin hydrochloride has been shown to have neuromuscular blocking properties that may enhance the action of other neuromuscular blocking agents. Therefore, Clindamycin Hydrochloride Oral Drops should be used with caution in animals receiving such agents.

Safety in gestating bitches and queens or breeding male dogs and cats has not been established.

ADVERSE REACTIONS

Side effects occasionally observed in either clinical trials or during clinical use were vomiting and diarrhea.

To report a suspected adverse reaction or to request a material safety data sheet (MSDS), call (888) 708-3326.

ACTIONS

Site and Mode of Action: Clindamycin is an inhibitor of protein synthesis in the bacterial cell. The site of binding appears to be in the 50S sub-unit of the ribosome. Binding occurs to the soluble RNA fraction of certain ribosomes, thereby inhibiting the binding of amino acids to those ribosomes. Clindamycin differs from cell wall inhibitors in that it causes irreversible modification of the protein- synthesizing subcellular elements at the ribosomal level.

MICROBIOLOGY

Microbiology: Clindamycin is a lincosaminide antimicrobial agent with activity against a wide variety of aerobic and anaerobic bacterial pathogens. Clindamycin is a bacteriostatic compound that inhibits bacterial protein synthesis by binding to the 50S ribosomal sub-unit. The minimum inhibitory concentrations (MICs) of Gram-positive and obligate anaerobic pathogens isolated from dogs and cats in the United States are presented in Table 1 and Table 2. Bacteria were isolated in 1998-1999. All MICs were performed in accordance with the National Committee for Clinical Laboratory Standards (NCCLS).

LABORATORY TESTS

Table 1. Clindamycin MIC Values (ug/mL) from Diagnostic Laboratory Survey Data Evaluating Canine Pathogens in the U.S. During 1998-99^1
Organism | Number of; Isolates | MIC50 | MIC85 | MIC90 | Range
Soft Tissue/Wound^2
Staphylococcus aureus | 17 | 0.5 | 0.5 | >4.0 | 0.25->4.0
Staphylococcus intermedius | 28 | 0.25 | 0.5 | >4.0 | 0.125->4.0
Staphylococcus spp. | 18 | 0.5 | 0.5 | >4.0 | 0.25->4.0
Beta-hemolytic streptococci | 46 | 0.5 | 0.5 | >4.0 | 0.25->4.0
Streptococcus spp. | 11 | 0.5 | >4.0 | >4.0 | 0.25->4.0
Osteomyelitis/Bone^3
Staphylococcus aureus | 20 | 0.5 | 0.5 | 0.5 | 0.5^4
Staphylococcus intermedius | 15 | 0.5 | >4.0 | >4.0 | 0.25->4.0
Staphylococcus spp. | 18 | 0.5 | >4.0 | >4.0 | 0.25->4.0
Beta-hemolytic streptococci | 21 | 0.5 | 2.0 | 2.0 | 0.25->4.0
Streptococcus spp. | 21 | >4.0 | >4.0 | >4.0 | 0.25->4.0
Dermal/Skin^5
Staphylococcus aureus | 25 | 0.5 | >4.0 | >4.0 | 0.25->4.0
Staphylococcus intermedius | 48 | 0.5 | >4.0 | >4.0 | 0.125->4.0
Staphlyococcus spp. | 32 | 0.5 | >4.0 | >4.0 | 0.25->4.0
Beta-hemolytic streptococci | 17 | 0.5 | 0.5 | 0.5 | 0.25-0.5

^1 The correlation between the in vitro susceptibility data and clinical response has not been determined.

^2 Soft Tissue/Wound: includes samples labeled wound, abscess, aspirate, exudates, draining tract, lesion, and mass

^3 Osteomyelitis/Bone: includes samples labeled bone, fracture, joint, tendon

^4 No range, all isolates yielded the same value

^5 Dermal/Skin: includes samples labeled skin, skin swab, biopsy, incision, lip

LABORATORY TESTS

Table 2. Clindamycin MIC Values (ug/mL) from Diagnostic Laboratory Survey Data Evaluating Feline Pathogens from Wound and Abscess Samples in the U.S. During 1998^1
Organism | Number of; Isolates | MIC50 | MIC90 | Range
Bacteroides/Prevotella | 30 | 0.06 | 4.0 | <0.015-4.0
Fusobacterium spp. | 17 | 0.25 | 0.25 | <0.015-0.5
Peptostreptococcus spp. | 18 | 0.13 | 0.5 | <0.015-8.0
Porphyromonas spp. | 13 | 0.06 | 0.25 | <0.015-8.0

^1 The correlation between the in vitro susceptibility data and clinical response has not been determined.

PHARMACOLOGY

Absorption: Clindamycin hydrochloride is rapidly absorbed from the canine and feline gastrointestinal tract.

Dog Serum Levels:

Serum levels at or above 0.5 μg/mL can be maintained by oral dosing at a rate of 5.0 mg/lb of clindamycin hydrochloride every 12 hours. This same study revealed that average peak serum concentrations of clindamycin occur 1 hour and 15 minutes after oral dosing. The elimination half-life for clindamycin in dog serum was approximately 5 hours. There was no bioactivity accumulation after a regimen of multiple oral doses in healthy dogs.

Cat Serum Levels:

Serum levels at or above 0.5 μg/mL can be maintained by oral dosing at a rate of 5.0 mg/lb of clindamycin hydrochloride every 24 hours. The average peak serum concentration of clindamycin occurs approximately 1 hour after oral dosing. The elimination half-life of clindamycin in feline serum is approximately 7.5 hours. In healthy cats, minimal accumulation occurs after multiple oral doses of clindamycin hydrochloride, and steady-state should be achieved by the third dose.

METABOLISM AND EXCRETION

Extensive studies of the metabolism and excretion of clindamycin hydrochloride administered orally in animals and humans have shown that unchanged drug and bioactive and bioinactive metabolites are excreted in urine and feces. Almost all of the bioactivity detected in serum after Clindamycin Hydrochloride Oral Drops product administration is due to the parent molecule (clindamycin). Urine bioactivity, however, reflects a mixture of clindamycin and active metabolites, especially N-demethyl clindamycin and clindamycin sulfoxide.

ANIMAL SAFETY SUMMARY

Rat and Dog Data: One year oral toxicity studies in rats and dogs at doses of 30, 100 and 300 mg/kg/day (13.6, 45.5 and 136.4 mg/lb/day) have shown clindamycin hydrochloride to be well tolerated. Differences did not occur in the parameters evaluated to assess toxicity when comparing groups of treated animals with contemporary controls. Rats administered clindamycin hydrochloride at 600 mg/kg/day (272.7 mg/lb/day) for six months tolerated the drug well; however, dogs orally dosed at 600 mg/kg/day (272.7 mg/lb/day) vomited, had anorexia, and subsequently lost weight. At necropsy these dogs had erosive gastritis and focal areas of necrosis of the mucosa of the gallbladder.

Safety in gestating bitches or breeding males has not been established.

ANIMAL SAFETY SUMMARY

Cat Data: The recommended daily therapeutic dose range for clindamycin hydrochloride (Clindamycin Hydrochloride Oral Drops) is 11 to 33 mg/kg/day (5 to 15 mg/lb/day) depending on the severity of the condition. Clindamycin hydrochloride (Clindamycin Hydrochloride Oral Drops) was tolerated with little evidence of toxicity in domestic shorthair cats when administered orally at 10x the minimum recommended therapeutic daily dose (11 mg/kg; 5 mg/lb) for 15 days, and at doses up to 5x the minimum recommended therapeutic dose for 42 days.

Gastrointestinal tract upset (soft feces to diarrhea) occurred in control and treated cats with emesis occurring at doses 3x or greater than the minimum recommended therapeutic dose (11 mg/kg/day; 5 mg/lb/day). Lymphocytic inflammation of the gallbladder was noted in a greater number of treated cats at the 110 mg/kg/day (50 mg/lb/day) dose level than for control cats. No other effects were noted. Safety in gestating queens or breeding male cats has not been established.

HOW SUPPLIED

ClindaCure® is available as 20 mL filled in 30 mL bottles (25 mg/mL) supplied in packers containing 12 cartoned bottles with direction labels and calibrated dosing droppers.

STORAGE

Store at controlled room temperature between 20° to 25° C (68° to 77° F) [see USP].

Keep container tightly closed when not in use.

Rev. 10-22

Distributed By:
VEDCO, INC.
St. Joseph, MO 64507